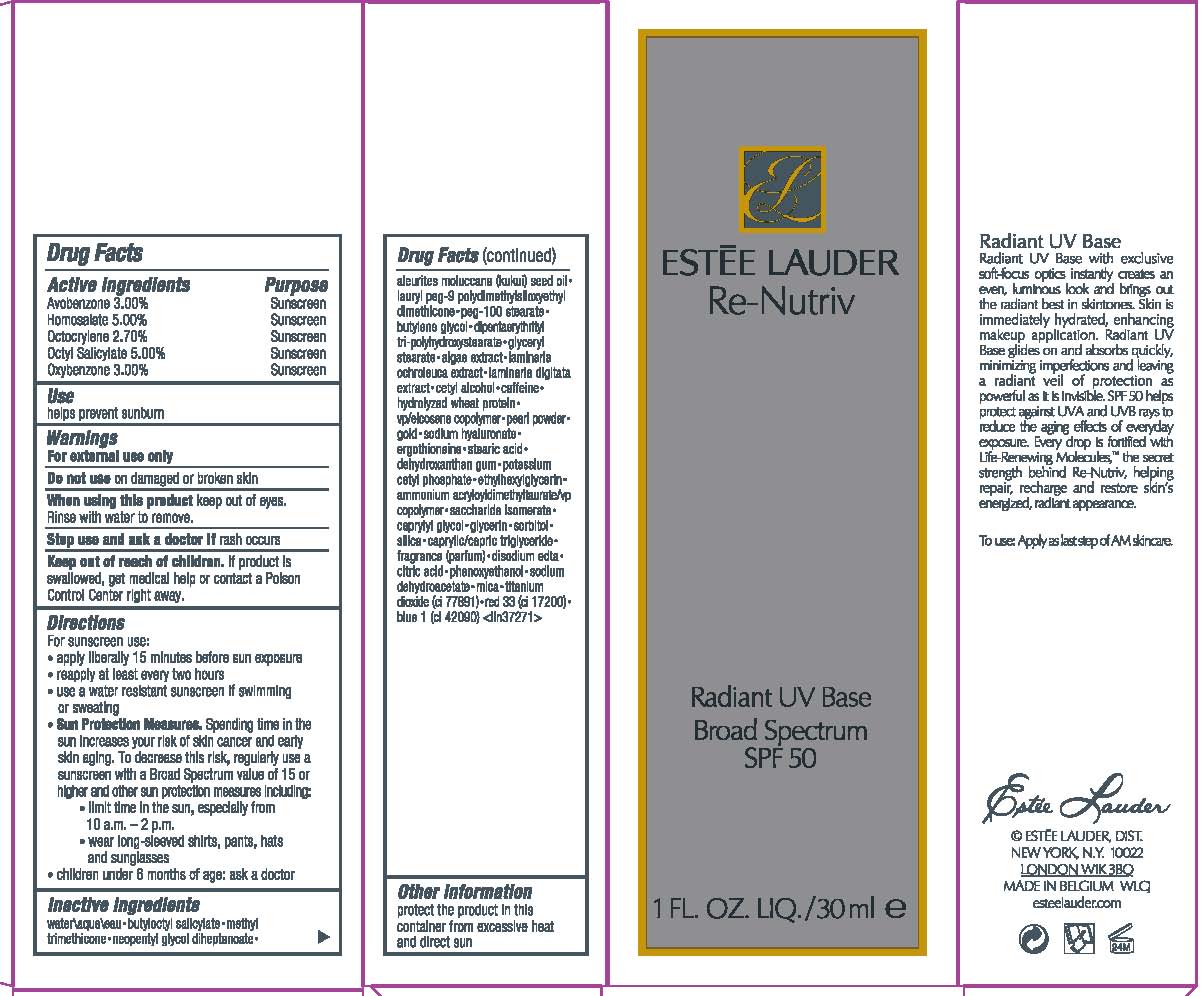 DRUG LABEL: RE NUTRIV RADIANT UV BASE
NDC: 11559-017 | Form: LOTION
Manufacturer: ESTEE LAUDER INC
Category: otc | Type: HUMAN OTC DRUG LABEL
Date: 20120424

ACTIVE INGREDIENTS: HOMOSALATE 5.0 mL/100 mL; OCTISALATE 5.0 mL/100 mL; AVOBENZONE 3.0 mL/100 mL; OXYBENZONE 3.0 nmol/100 mL; OCTOCRYLENE 2.7 mL/100 mL
INACTIVE INGREDIENTS: WATER; BUTYLOCTYL SALICYLATE; METHYL TRIMETHICONE; NEOPENTYL GLYCOL DIHEPTANOATE; KUKUI NUT; PEG-100 STEARATE; BUTYLENE GLYCOL; GLYCERYL MONOSTEARATE; NORI; LAMINARIA DIGITATA; CETYL ALCOHOL; CAFFEINE; HYDROLYZED WHEAT PROTEIN (ENZYMATIC, 3000 MW); CALCIUM CARBONATE; HYALURONATE SODIUM; ERGOTHIONEINE; STEARIC ACID; XANTHAN GUM; POTASSIUM CETYL PHOSPHATE; SACCHARIDE ISOMERATE; CAPRYLYL GLYCOL; GLYCERIN; SORBITOL; SILICON DIOXIDE; MEDIUM-CHAIN TRIGLYCERIDES; EDETATE DISODIUM; CITRIC ACID MONOHYDRATE; PHENOXYETHANOL; SODIUM DEHYDROACETATE; MICA; TITANIUM DIOXIDE; D&C RED NO. 33; FD&C BLUE NO. 1

DRUG FACTS

ACTIVE INGREDIENTS:

AVOBENZONE 3.00%

HOMOSALATE 5.00%

OCTOCRYLENE 2.70%

OCTISALATE 5.00%

OXYBENZONE 3.00%

PURPOSE

SUNSCREEN

USE

HELPS PREVENT SUNBURN

WARNINGS

FOR EXTERNAL USE ONLY

Do not use on damaged or broken skin

When using this product keep out of eyes. Rinse with water to remove.

Stop use and ask a doctor if rash occurs

Keep out of reach of children.

If product is swallowed, get medical help or contact a Poison Control Center right away.

DIRECTIONS

For sunscreen use:
* apply liberally 15 minutes before sun exposure
* reapply at least every two hours
* use a water resistant sunscreen if swimming or sweating
* Sun Protection Measures.
Spending time in the sun increases your risk of skin cancer and early skin aging. To decrease this risk, regularly use a sunscreen with a Broad Spectrum SPF value of 15 or higher and other sun protection measures including:
o limit time in the sun, especially from 10 a.m.–2 p.m.
o wear long-sleeved shirts, pants, hats and sunglasses
* children under 6 months of age: ask a doctor

INACTIVE INGREDIENTS

WATER\AQUA\EAU [] BUTYLOCTYL SALICYLATE [] METHYL TRIMETHICONE [] NEOPENTYL GLYCOL DIHEPTANOATE [] ALEURITES MOLUCCANA (KUKUI) SEED OIL [] LAURYL PEG-9 POLYDIMETHYLSILOXYETHYL DIMETHICONE [] PEG-100 STEARATE [] BUTYLENE GLYCOL [] DIPENTAERYTHRITYL TRI-POLYHYDROXYSTEARATE [] GLYCERYL STEARATE [] ALGAE EXTRACT [] LAMINARIA OCHROLEUCA EXTRACT [] LAMINARIA DIGITATA EXTRACT [] CETYL ALCOHOL [] CAFFEINE [] HYDROLYZED WHEAT PROTEIN [] VP/EICOSENE COPOLYMER [] PEARL POWDER [] GOLD [] SODIUM HYALURONATE [] ERGOTHIONEINE [] STEARIC ACID [] DEHYDROXANTHAN GUM [] POTASSIUM CETYL PHOSPHATE [] ETHYLHEXYLGLYCERIN [] AMMONIUM ACRYLOYLDIMETHYLTAURATE/VP COPOLYMER [] SACCHARIDE ISOMERATE [] CAPRYLYL GLYCOL [] GLYCERIN [] SORBITOL [] SILICA [] CAPRYLIC/CAPRIC TRIGLYCERIDE [] FRAGRANCE (PARFUM) [] DISODIUM EDTA [] CITRIC ACID [] PHENOXYETHANOL [] SODIUM DEHYDROACETATE [] MICA [] TITANIUM DIOXIDE (CI 77891) [] RED 33 (CI 17200) [] BLUE 1 (CI 42090)

OTHER INFORMATION

protect the product in this container from excessive heat and direct sun

PACKAGE LABEL

PRINCIPAL DISPLAY PANEL:

ESTEE LAUDER

RE-NUTRIV

RADIANT UV BASE

BROAD SPECTRUM

SPF 50

1FL OZ LIQ / 30 ML
ESTEE LAUDER DIST
NY, NY 10022